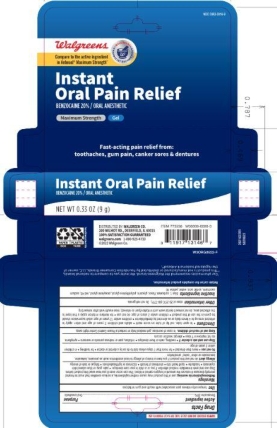 DRUG LABEL: NBE Anbesol
NDC: 0363-0316 | Form: GEL
Manufacturer: Walgreens
Category: otc | Type: HUMAN OTC DRUG LABEL
Date: 20251121

ACTIVE INGREDIENTS: BENZOCAINE 20 g/100 g
INACTIVE INGREDIENTS: SORBIC ACID; PROPYLENE GLYCOL; WATER; FD&C RED NO. 40; D&C YELLOW NO. 10; FD&C BLUE NO. 1; SACCHARIN SODIUM; CARBOXYPOLYMETHYLENE; POLYETHYLENE GLYCOL, UNSPECIFIED; GLYCERIN

5820622 Walgreens NBE Anbesol Gel

ACTIVE INGREDIENT

Benzocaine 20%

PURPOSE

Oral anesthetic

INDICATIONS AND USAGE

temporarily relieves pain associated with mouth and gum irritations

WARNINGS

Methemoglobinemia warning: use of this product may cause methemoglobinemia, a serious condition that must be treated promptly because it reduces the amount of oxygen carried in blood. This can occur even if you have used this product before. Stop use and seek immediate medical attention if you or a child in your care develops: * pale, gray, or blue colored skin (cyanosis) * headache * rapid heart rate * shortness of breath * dizziness or lightheadedness * fatigue or lack of energy

Allergy alert: do not use this product if you have a history of allergy to local anesthetics such as procaine, butacaine, benzocaine, or other "caine" anesthetics

Do not use * more than directed * for more than 7 days unless told to do so by a dentist or doctor * for teething * in children under 2 years of age

Stop use and ask a doctor if * swelling, rash or fever develops * irritation, pain or redness persists or worsens * symptoms do not improve in 7 days * allergic reaction occurs

Keep out of reach of children. In case of overdose, get medical help or contact a Poison Control Center right away.

DOSAGE AND ADMINISTRATION

to open tube, cut tip of tube on score mark * adults and children 2 years of age and older: apply to affected area up to 4 times daily or as directed by a dentist/doctor * children under 12 years of age: adult supervision should be given in the use of this product * children under 2 years of age: do not use * for denture irritation apply a thin layer to the affected area; do not reinsert dental work until irritation/pain is relieved; rinse mouth well after reinserting

OTHER SAFETY INFORMATION

store at 20-25C (68-77F). Do not refrigerate.

INACTIVE INGREDIENT

blue 1, carbomer, flavor, glycerin, polyethylene glycol, propylene glycol, red 40, sodium saccharin, sorbic acid, water, yellow 10